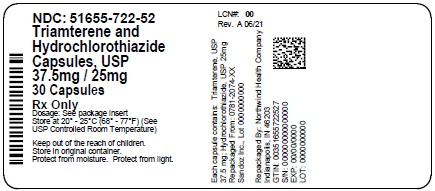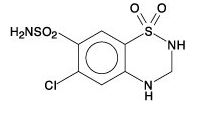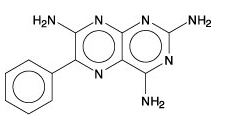 DRUG LABEL: Triamterene and Hydrochlorothiazide
NDC: 51655-722 | Form: CAPSULE
Manufacturer: Northwind Health Company, LLC
Category: prescription | Type: HUMAN PRESCRIPTION DRUG LABEL
Date: 20260101

ACTIVE INGREDIENTS: TRIAMTERENE 37.5 mg/1 1; HYDROCHLOROTHIAZIDE 25 mg/1 1
INACTIVE INGREDIENTS: ANHYDROUS LACTOSE; CITRIC ACID MONOHYDRATE; D&C YELLOW NO. 10; FD&C BLUE NO. 1; FD&C BLUE NO. 2; FD&C RED NO. 40; FERROSOFERRIC OXIDE; GELATIN, UNSPECIFIED; GLYCINE; MAGNESIUM STEARATE; POLYSORBATE 80; POVIDONE, UNSPECIFIED; PROPYLENE GLYCOL; SHELLAC; SODIUM STARCH GLYCOLATE TYPE A POTATO; STARCH, CORN; TITANIUM DIOXIDE

Triamterene and Hydrochlorothiazide Capsules, USP

DESCRIPTION

Triamterene, USP is an antikaliuretic agent and hydrochlorothiazide, USP is a diuretic/antihypertensive agent.

At 50°C, triamterene, USP is practically insoluble in water (less than 0.1%). It is soluble in formic acid, sparingly soluble in methoxyethanol, and very slightly soluble in alcohol.

Triamterene, USP is 2,4,7-triamino-6-phenylpteridine with a chemical formula of C12H11N7and a molecular weight of 253.27. The structural formula for triamterene is:

Hydrochlorothiazide, USP is slightly soluble in water. It is soluble in dilute ammonia, dilute aqueous sodium hydroxide, and dimethylformamide. It is sparingly soluble in methanol.

Hydrochlorothiazide, USP is 6-chloro-3,4-dihydro-2H-1,2, 4-benzothiadiazine-7-sulfonamide 1,1-dioxide with a chemical formula of C7H8ClN3O4S2and a molecular weight of 297.75. The structural formula for hydrochlorothiazide is:

Each capsule, for oral administration, contains 37.5 mg triamterene, USP and 25 mg hydrochlorothiazide, USP.

The 37.5 mg triamterene, USP and 25 mg hydrochlorothiazide, USP capsule inactive ingredients include: citric acid, corn starch, glycine, anhydrous lactose, magnesium stearate, Polysorbate 80, povidone, and sodium starch glycolate. The capsule shells and imprinting inks contain: D & C Yellow #10 Aluminum Lake, FD & C Blue #1 Aluminum Lake, FD & C Blue #2 Aluminum Lake, FD & C Red #40 Aluminum Lake, gelatin, pharmaceutical glaze, propylene glycol, synthetic black iron oxide, and titanium dioxide.

The 37.5 mg triamterene, USP and 25 mg hydrochlorothiazide, USP capsules meets USP Dissolution Test 3.

CLINICAL PHARMACOLOGY

Triamterene and hydrochlorothiazide is a diuretic/antihypertensive drug product that combines natriuretic and antikaliuretic effects. Each component complements the action of the other. The hydrochlorothiazide component blocks the reabsorption of sodium and chloride ions, and thereby increases the quantity of sodium traversing the distal tubule and the volume of water excreted. A portion of the additional sodium presented to the distal tubule is exchanged there for potassium and hydrogen ions. With continued use of hydrochlorothiazide and depletion of sodium, compensatory mechanisms tend to increase this exchange and may produce excessive loss of potassium, hydrogen, and chloride ions. Hydrochlorothiazide also decreases the excretion of calcium and uric acid, may increase the excretion of iodide, and may reduce glomerular filtration rate. The exact mechanism of the antihypertensive effect of hydrochlorothiazide is not known.

The triamterene component of triamterene and hydrochlorothiazide capsule exerts its diuretic effect on the distal renal tubule to inhibit the reabsorption of sodium in exchange for potassium and hydrogen ions. Its natriuretic activity is limited by the amount of sodium reaching its site of action. Although it blocks the increase in this exchange that is stimulated by mineralocorticoids (chiefly aldosterone), it is not a competitive antagonist of aldosterone and its activity can be demonstrated in adrenalectomized rats and patients with Addison’s disease. As a result, the dose of triamterene required is not proportionally related to the level of mineralocorticoid activity but is dictated by the response of the individual patients and the kaliuretic effect of concomitantly administered drugs. By inhibiting the distal tubular exchange mechanism, triamterene maintains or increases the sodium excretion and reduces the excess loss of potassium, hydrogen, and chloride ions induced by hydrochlorothiazide. As with hydrochlorothiazide, triamterene may reduce glomerular filtration and renal plasma flow. Via this mechanism, it may reduce uric acid excretion although it has no tubular effect on uric acid reabsorption or secretion. Triamterene does not affect calcium excretion. No predictable antihypertensive effect has been demonstrated for triamterene.

Duration of diuretic activity and effective dosage range of the hydrochlorothiazide and triamterene components are similar. Onset of diuresis with triamterene and hydrochlorothiazide takes place within one hour, peaks at two to three hours, and tapers off during the subsequent seven to nine hours.

Triamterene and hydrochlorothiazide capsules are well absorbed.

Upon administration of a single oral dose to fasted normal male volunteers, mean pharmacokinetic parameters were determined (Table 1).

Table 1. Mean Pharmacokinetic Parameters after Single Oral Dose in Fasted Male Volunteers [AUC (0-48), C max, T max, and Ae represent area under the plasma concentration versus time plot, maximum plasma concentration, time to reach C max, and amount excreted in urine over 48 hours.]
 | AUC(0-48); ng*h/mL; (± SD) | Cmax; ng/mL; (± SD) | Median; Tmax; h | Ae; Mg; (± SD)
Triamterene | 148.7 (87.9) | 46.4 (29.4) | 1.1 | 2.7 (1.4)
Hydroxytriamterene; sulfate | 1,865 (471) | 720 (364) | 1.3 | 19.7 (6.1)
Hydrochlorothiazide | 834 (177) | 135.1 (35.7) | 2.0 | 14.3 (3.8)

A capsule of triamterene and hydrochlorothiazide is bioequivalent to a single entity 25-mg hydrochlorothiazide tablet and 37.5-mg triamterene capsule used in the double-blind clinical trial below (see CLINICAL TRIALS).

In a limited study involving 12 subjects, coadministration of triamterene and hydrochlorothiazide capsule with a high-fat meal resulted in: (1) an increase in the mean bioavailability of triamterene by about 67% (90% confidence interval = 0.99, 1.90), p-hydroxytriamterene sulfate by about 50% (90% confidence interval = 1.06, 1.77), hydrochlorothiazide by about 17% (90% confidence interval = 0.90, 1.34); (2) increases in the peak concentrations of triamterene and p-hydroxytriamterene; and (3) a delay of up to 2 hours in the absorption of the active constituents.

CLINICAL TRIALS

A placebo-controlled, double-blind trial was conducted to evaluate the efficacy of triamterene and hydrochlorothiazide capsules. This trial demonstrated that triamterene and hydrochlorothiazide capsules (25 mg hydrochlorothiazide/37.5 mg triamterene) was effective in controlling blood pressure while reducing the incidence of hydrochlorothiazide-induced hypokalemia. This trial involved 636 patients with mild to moderate hypertension controlled by hydrochlorothiazide 25 mg daily and who had hypokalemia (serum potassium <3.5 mEq/L) secondary to the hydrochlorothiazide. Patients were randomly assigned to 4 weeks’ treatment with once-daily regimens of 25 mg hydrochlorothiazide plus placebo, or 25 mg hydrochlorothiazide combined with one of the following doses of triamterene: 25 mg, 37.5 mg, 50 mg, or 75 mg.

Blood pressure and serum potassium were monitored at baseline and throughout the trial. All five treatment groups had similar mean blood pressure and serum potassium concentrations at baseline (mean systolic blood pressure range: 137 ± 14 mmHg to 140 ± 16 mmHg; mean diastolic blood pressure range: 86 ± 9 mmHg to 88 ± 8 mmHg; mean serum potassium range: 2.3 to 3.4 mEq/L with the majority of patients having values between 3.1 and 3.4 mEq/L).

While all triamterene regimens reversed hypokalemia, at Week 4 the 37.5-mg regimen proved optimal compared with the other tested regimens. On this regimen, 81% of the patients had a significant (P<0.05) reversal of hypokalemia vs. 59% of patients on the placebo/hydrochlorothiazide regimen. The mean serum potassium concentration on 37.5 mg triamterene went from 3.2 ± 0.2 mEq/L at baseline to 3.7 ± 0.3 mEq/L at Week 4, a significantly greater (P<0.05) improvement than that achieved with placebo/hydrochlorothiazide (i.e., 3.2 ± 0.2 mEq/L at baseline and 3.5 ± 0.4 mEq/L at Week 4). Also, 51% of patients in the 37.5-mg triamterene group had an increase in serum potassium of ≥0.5 mEq/L at Week 4 vs. 33% in the placebo group. The 37.5-mg triamterene/25-mg hydrochlorothiazide regimen also maintained control of blood pressure; mean supine systolic blood pressure at Week 4 was 138 ± 21 mmHg while mean supine diastolic blood pressure was 87 ± 13 mmHg.

INDICATIONS AND USAGE

This fixed combination drug is not indicated for the initial therapy of edema or hypertension except in individuals in whom the development of hypokalemia cannot be risked.

Triamterene and hydrochlorothiazide is indicated for the treatment of hypertension or edema in patients who develop hypokalemia on hydrochlorothiazide alone.

Triamterene and hydrochlorothiazide is also indicated for those patients who require a thiazide diuretic and in whom the development of hypokalemia cannot be risked.

Triamterene and hydrochlorothiazide may be used alone or as an adjunct to other antihypertensive drugs, such as beta-blockers. Since triamterene and hydrochlorothiazide may enhance the action of these agents, dosage adjustments may be necessary.

Usage in Pregnancy

The routine use of diuretics in an otherwise healthy woman is inappropriate and exposes mother and fetus to unnecessary hazard. Diuretics do not prevent development of toxemia of pregnancy, and there is no satisfactory evidence that they are useful in the treatment of developed toxemia.

Edema during pregnancy may arise from pathological causes or from the physiologic and mechanical consequences of pregnancy. Diuretics are indicated in pregnancy when edema is due to pathologic causes, just as they are in the absence of pregnancy. Dependent edema in pregnancy resulting from restriction of venous return by the expanded uterus is properly treated through elevation of the lower extremities and use of support hose; use of diuretics to lower intravascular volume in this case is illogical and unnecessary. There is hypervolemia during normal pregnancy which is harmful to neither the fetus nor the mother (in the absence of cardiovascular disease), but which is associated with edema, including generalized edema in the majority of pregnant women. If this edema produces discomfort, increased recumbency will often provide relief. In rare instances this edema may cause extreme discomfort which is not relieved by rest. In these cases, a short course of diuretics may provide relief and may be appropriate.

CONTRAINDICATIONS

Antikaliuretic Therapy and Potassium Supplementation

Triamterene and hydrochlorothiazide should not be given to patients receiving other potassium-sparing agents such as spironolactone, amiloride, or other formulations containing triamterene. Concomitant potassium-containing salt substitutes should also not be used.

Potassium supplementation should not be used with triamterene and hydrochlorothiazide except in severe cases of hypokalemia. Such concomitant therapy can be associated with rapid increases in serum potassium levels. If potassium supplementation is used, careful monitoring of the serum potassium level is necessary.

Impaired Renal Function

Triamterene and hydrochlorothiazide is contraindicated in patients with anuria, acute and chronic renal insufficiency, or significant renal impairment.

Hypersensitivity

Hypersensitivity to either drug in the preparation or to other sulfonamide-derived drugs is a contraindication.

Hyperkalemia

Triamterene and hydrochlorothiazide should not be used in patients with pre-existing elevated serum potassium.

WARNINGS

Hyperkalemia

Abnormal elevation of serum potassium levels (≥5.5 mEq/liter) can occur with all potassium-sparing diuretic combinations, including triamterene and hydrochlorothiazide. Hyperkalemia is more likely to occur in patients with renal impairment and diabetes (even without evidence of renal impairment) and in the elderly or severely ill. Since uncorrected hyperkalemia may be fatal, serum potassium levels must be monitored at frequent intervals especially in patients first receiving triamterene and hydrochlorothiazide, when dosages are changed, or with any illness that may influence renal function.

If hyperkalemia is suspected (warning signs include paresthesias, muscular weakness, fatigue, flaccid paralysis of the extremities, bradycardia, and shock), an electrocardiogram (ECG) should be obtained. However, it is important to monitor serum potassium levels because hyperkalemia may not be associated with ECG changes.

If hyperkalemia is present, triamterene and hydrochlorothiazide should be discontinued immediately and a thiazide alone should be substituted. If the serum potassium exceeds 6.5 mEq/L, more vigorous therapy is required. The clinical situation dictates the procedures to be employed. These include the intravenous administration of calcium chloride solution, sodium bicarbonate solution, and/or the oral or parenteral administration of glucose with a rapid-acting insulin preparation. Cationic exchange resins such as sodium polystyrene sulfonate may be orally or rectally administered. Persistent hyperkalemia may require dialysis.

The development of hyperkalemia associated with potassium-sparing diuretics is accentuated in the presence of renal impairment (see CONTRAINDICATIONS). Patients with mild renal functional impairment should not receive this drug without frequent and continuing monitoring of serum electrolytes. Cumulative drug effects may be observed in patients with impaired renal function. The renal clearances of hydrochlorothiazide and the pharmacologically active metabolite of triamterene, the sulfate ester of hydroxytriamterene, have been shown to be reduced and the plasma levels increased following administration of triamterene and hydrochlorothiazide to elderly patients and patients with impaired renal function.

Hyperkalemia has been reported in diabetic patients with the use of potassium-sparing agents even in the absence of apparent renal impairment. Accordingly, serum electrolytes must be frequently monitored if triamterene and hydrochlorothiazide is used in diabetic patients.

Metabolic or Respiratory Acidosis

Potassium-sparing therapy should also be avoided in severely ill patients in whom respiratory or metabolic acidosis may occur. Acidosis may be associated with rapid elevations in serum potassium levels. If triamterene and hydrochlorothiazide is employed, frequent evaluations of acid/base balance and serum electrolytes are necessary.

Acute Myopia and Secondary Angle-Closure Glaucoma

Hydrochlorothiazide, a sulfonamide, can cause an idiosyncratic reaction, resulting in acute transient myopia and acute angle-closure glaucoma. Symptoms include acute onset of decreased visual acuity or ocular pain and typically occur within hours to weeks of drug initiation. Untreated acute angle-closure glaucoma can lead to permanent vision loss. The primary treatment is to discontinue hydrochlorothiazide as rapidly as possible. Prompt medical or surgical treatments may need to be considered if the intraocular pressure remains uncontrolled. Risk factors for developing acute angle-closure glaucoma may include a history of sulfonamide or penicillin allergy.

PRECAUTIONS

Diabetes

Caution should be exercised when administering triamterene and hydrochlorothiazide to patients with diabetes, since thiazides may cause hyperglycemia, glycosuria, and alter insulin requirements in diabetes. Also, diabetes mellitus may become manifest during thiazide administration.

Impaired Hepatic Function

Thiazides should be used with caution in patients with impaired hepatic function. They can precipitate hepatic coma in patients with severe liver disease. Potassium depletion induced by the thiazide may be important in this connection. Administer triamterene and hydrochlorothiazide cautiously and be alert for early signs of impending coma such as confusion, drowsiness, and tremor; if mental confusion increases, discontinue triamterene and hydrochlorothiazide for a few days. Attention must be given to other factors that may precipitate hepatic coma, such as blood in the gastrointestinal tract or pre-existing potassium depletion.

Hypokalemia

Hypokalemia is uncommon with triamterene and hydrochlorothiazide; but, should it develop, corrective measures should be taken such as potassium supplementation or increased intake of potassium-rich foods. Institute such measures cautiously with frequent determinations of serum potassium levels, especially in patients receiving digitalis or with a history of cardiac arrhythmias. If serious hypokalemia (serum potassium < 3.0 mEq/L) is demonstrated by repeat serum potassium determinations, triamterene and hydrochlorothiazide should be discontinued and potassium chloride supplementation initiated. Less serious hypokalemia should be evaluated with regard to other coexisting conditions and treated accordingly.

Electrolyte Imbalance

Electrolyte imbalance, often encountered in conditions such as heart failure, renal disease, or cirrhosis of the liver, may also be aggravated by diuretics and should be considered during therapy with triamterene and hydrochlorothiazide when using high doses for prolonged periods or in patients on a salt-restricted diet. Serum determinations of electrolytes should be performed and are particularly important if the patient is vomiting excessively or receiving fluids parenterally. Possible fluid and electrolyte imbalance may be indicated by warning signs such as: dry mouth, thirst, weakness, lethargy, drowsiness, restlessness, muscle pain or cramps, muscular fatigue, hypotension, oliguria, tachycardia, and gastrointestinal symptoms.

Hypochloremia

Although any chloride deficit is generally mild and usually does not require specific treatment except under extraordinary circumstances (as in liver disease or renal disease), chloride replacement may be required in the treatment of metabolic alkalosis. Dilutional hyponatremia may occur in edematous patients in hot weather; appropriate therapy is water restriction, rather than administration of salt, except in rare instances when the hyponatremia is life threatening. In actual salt depletion, appropriate replacement is the therapy of choice.

Renal Stones

Triamterene has been found in renal stones in association with the other usual calculus components. Triamterene and hydrochlorothiazide should be used with caution in patients with a history of renal stones.

Laboratory Tests

Serum Potassium

The normal adult range of serum potassium is 3.5 to 5.0 mEq/L with 4.5 mEq often being used for a reference point. If hypokalemia should develop, corrective measures should be taken such as potassium supplementation or increased dietary intake of potassium-rich foods.

Institute such measures cautiously with frequent determinations of serum potassium levels. Potassium levels persistently above 6 mEq/L require careful observation and treatment. Serum potassium levels do not necessarily indicate true body potassium concentration. A rise in plasma pH may cause a decrease in plasma potassium concentration and an increase in the intracellular potassium concentration. Discontinue corrective measures for hypokalemia immediately if laboratory determinations reveal an abnormal elevation of serum potassium.

Discontinue triamterene and hydrochlorothiazide and substitute a thiazide diuretic alone until potassium levels return to normal.

Serum Creatinine and Blood Urea Nitrogen

Triamterene and hydrochlorothiazide may produce an elevated blood urea nitrogen (BUN) level, creatinine level, or both. This apparently is secondary to a reversible reduction of glomerular filtration rate or a depletion of intravascular fluid volume (prerenal azotemia) rather than renal toxicity; levels usually return to normal when triamterene and hydrochlorothiazide is discontinued. If azotemia increases, discontinue triamterene and hydrochlorothiazide. Periodic BUN or serum creatinine determinations should be made, especially in elderly patients and in patients with suspected or confirmed renal insufficiency.

Serum Protein-Bound Iodine

Thiazide may decrease serum protein-bound iodine (PBI) levels without sign of thyroid disturbance.

Parathyroid Function

Thiazides should be discontinued before carrying out tests for parathyroid function. Calcium excretion is decreased by thiazides. Pathologic changes in the parathyroid glands with hypercalcemia and hypophosphatemia have been observed in a few patients on prolonged thiazide therapy. The common complications of hyperparathyroidism such as bone resorption and peptic ulceration have not been seen.

Drug Interactions

Angiotensin-Converting Enzyme Inhibitors

Potassium-sparing agents should be used with caution in conjunction with angiotensin-converting enzyme (ACE) inhibitors due to an increased risk of hyperkalemia.

Oral Hypoglycemic Drugs

Concurrent use with chlorpropamide may increase the risk of severe hyponatremia.

Nonsteroidal Anti-Inflammatory Drugs

A possible interaction resulting in acute renal failure has been reported in a few patients on triamterene and hydrochlorothiazide when treated with indomethacin, a nonsteroidal anti-inflammatory agent. Caution is advised in administering nonsteroidal anti-inflammatory agents with triamterene and hydrochlorothiazide.

Lithium

Lithium generally should not be given with diuretics because they reduce its renal clearance and increase the risk of lithium toxicity. Read prescribing information for lithium preparations before use of such concomitant therapy with triamterene and hydrochlorothiazide.

Surgical Considerations

Thiazides have been shown to decrease arterial responsiveness to norepinephrine (an effect attributed to loss of sodium). This diminution is not sufficient to preclude effectiveness of the pressor agent for therapeutic use. Thiazides have also been shown to increase the paralyzing effect of nondepolarizing muscle relaxants such as tubocurarine (an effect attributed to potassium loss); consequently, caution should be observed in patients undergoing surgery.

Other Considerations

Concurrent use of hydrochlorothiazide with amphotericin B or corticosteroids or corticotropin (ACTH) may intensify electrolyte imbalance, particularly hypokalemia, although the presence of triamterene minimizes the hypokalemic effect.

Thiazides may add to or potentiate the action of other antihypertensive drugs. See INDICATIONS AND USAGEfor concomitant use with other antihypertensive drugs.

The effect of oral anticoagulants may be decreased when used concurrently with hydrochlorothiazide; dosage adjustments may be necessary.

Triamterene and hydrochlorothiazide may raise the level of blood uric acid; dosage adjustments of antigout medication may be necessary to control hyperuricemia and gout.

The following agents given together with triamterene may promote serum potassium accumulation and possibly result in hyperkalemia because of the potassium-sparing nature of triamterene, especially in patients with renal insufficiency: blood from blood bank (may contain potassium up to 30 mEq/L of plasma or up to 65 mEq/L of whole blood when stored for more than 10 days); low-salt milk (may contain potassium up to 60 mEq/L); potassium-containing medications (such as parenteral penicillin G potassium); salt substitutes (most contain substantial amounts of potassium).

Exchange resins, such as sodium polystyrene sulfonate, whether administered orally or rectally, reduce serum potassium levels by sodium replacement of the potassium; fluid retention may occur in some patients because of the increased sodium intake.

Chronic or overuse of laxatives may reduce serum potassium levels by promoting excessive potassium loss from the intestinal tract; laxatives may interfere with the potassium-retaining effects of triamterene.

The effectiveness of methenamine may be decreased when used concurrently with hydrochlorothiazide because of alkalinization of the urine.

Information for Patients

Non-Melanoma Skin Cancer

Instruct patients taking hydrochlorothiazide to protect skin from the sun and undergo regular skin cancer screening.

Drug/Laboratory Test Interactions

Triamterene and quinidine have similar fluorescence spectra; thus, triamterene and hydrochlorothiazide will interfere with the fluorescent measurement of quinidine.

Carcinogenesis, Mutagenesis, Impairment of Fertility

Carcinogenesis

Long-term studies have not been conducted with the triamterene and hydrochlorothiazide combination, or with triamterene alone.

Hydrochlorothiazide

Two-year feeding studies in mice and rats, conducted under the auspices of the National Toxicology Program (NTP) treated mice and rats with doses of hydrochlorothiazide up to 600 and 100 mg/kg/day, respectively. On a body-weight basis, these doses are 600 times (in mice) and 100 times (in rats) the maximum recommended human dose (MRHD) for the hydrochlorothiazide component of triamterene and hydrochlorothiazide capsules at 50 mg/day (or 1.0 mg/kg/day based on 50-kg individuals). On the basis of body surface area, these doses are 56 times (in mice) and 21 times (in rats) the MRHD. These studies uncovered no evidence of carcinogenic potential of hydrochlorothiazide in rats or female mice, but there was equivocal evidence of hepatocarcinogenicity in male mice.

Mutagenesis

Studies of the mutagenic potential of the triamterene and hydrochlorothiazide combination or of triamterene alone have not been performed.

Hydrochlorothiazide

Hydrochlorothiazide was not genotoxic in in vitroassays using strains TA 98, TA 100, TA 1535, TA 1537, and TA 1538 of Salmonella typhimurium(the Ames test); in the Chinese Hamster Ovary (CHO) test for chromosomal aberrations; or in in vivoassays using mouse germinal cell chromosomes, Chinese hamster bone marrow chromosomes, and the Drosophilasex-linked recessive lethal trait gene. Positive test results were obtained in the in vitroCHO Sister Chromatid Exchange (clastogenicity) test and in the mouse Lymphoma Cell (mutagenicity) assays, using concentrations of hydrochlorothiazide of 43 to 1,300 mcg/mL. Positive test results were also obtained in the Aspergillus nidulansnondisjunction assay, using an unspecified concentration of hydrochlorothiazide.

Impairment of Fertility

Studies of the effects of the triamterene and hydrochlorothiazide combination or of triamterene alone on animal reproductive function have not been conducted.

Hydrochlorothiazide

Hydrochlorothiazide had no adverse effects on the fertility of mice and rats of either sex in studies wherein these species were exposed, via their diet, to doses of up to 100 and 4 mg/kg/day, respectively, prior to mating and throughout gestation. Corresponding multiples of the MRHD are 100 (mice) and 4 (rats) on the basis of body weight and 9.4 (mice) and 0.8 (rats) on the basis of body surface area.

Pregnancy

Teratogenic Effects

Triamterene and Hydrochlorothiazide

Animal reproduction studies to determine the potential for fetal harm by triamterene and hydrochlorothiazide have not been conducted. However, a One Generation Study in the rat approximated composition of triamterene and hydrochlorothiazide by using a 1:1 ratio of triamterene to hydrochlorothiazide (30:30 mg/kg/day); there was no evidence of teratogenicity at those doses which were, on a body-weight basis, 15 and 30 times, respectively, the MRHD, and on the basis of body surface area, 3.1 and 6.2 times, respectively, the MRHD.

The safe use of triamterene and hydrochlorothiazide in pregnancy has not been established since there are no adequate and well-controlled studies with triamterene and hydrochlorothiazide in pregnant women. Triamterene and hydrochlorothiazide should be used during pregnancy only if the potential benefit justifies the risk to the fetus.

Triamterene

Reproduction studies have been performed in rats at doses as high as 20 times the MRHD on the basis of body weight and 6 times the human dose on the basis of body surface area without evidence of harm to the fetus due to triamterene.

Because animal reproduction studies are not always predictive of human response, this drug should be used during pregnancy only if clearly needed.

Hydrochlorothiazide

Hydrochlorothiazide was orally administered to pregnant mice and rats during respective periods of major organogenesis at doses up to 3,000 and 1,000 mg/kg/day, respectively. At these doses, which are multiples of the MRHD equal to 3,000 for mice and 1,000 for rats, based on body weight, and equal to 282 for mice and 206 for rats, based on body surface area, there was no evidence of harm to the fetus.

There are, however, no adequate and well-controlled studies in pregnant women. Because animal reproduction studies are not always predictive of human response, this drug should be used during pregnancy only if clearly needed.

Nonteratogenic Effects

Thiazides and triamterene have been shown to cross the placental barrier and appear in cord blood. The use of thiazides and triamterene in pregnant women requires that the anticipated benefit be weighed against possible hazards to the fetus. These hazards include fetal or neonatal jaundice, pancreatitis, thrombocytopenia, and possible other adverse reactions which have occurred in the adult.

Nursing Mothers

Thiazides and triamterene in combination have not been studied in nursing mothers. Triamterene appears in animal milk; this may occur in humans. Thiazides are excreted in human breast milk. If use of the combination drug product is deemed essential, the patient should stop nursing.

Pediatric Use

Safety and effectiveness in pediatric patients have not been established.

ADVERSE REACTIONS

Adverse effects are listed in decreasing order of severity.

Hypersensitivity

Anaphylaxis, rash, urticaria, subacute cutaneous lupus erythematosus-like reactions, photosensitivity.

Cardiovascular

Arrhythmia, postural hypotension.

Metabolic

Diabetes mellitus, hyperkalemia, hypokalemia, hyponatremia, acidosis, hypercalcemia, hyperglycemia, glycosuria, hyperuricemia, hypochloremia.

Gastrointestinal

Jaundice and/or liver enzyme abnormalities, pancreatitis, nausea and vomiting, diarrhea, constipation, abdominal pain.

Renal

Acute renal failure (one case of irreversible renal failure has been reported), interstitial nephritis, renal stones composed primarily of triamterene, elevated BUN and serum creatinine, abnormal urinary sediment.

Hematologic

Leukopenia, thrombocytopenia and purpura, megaloblastic anemia.

Musculoskeletal

Muscle cramps.

Central Nervous System

Weakness, fatigue, dizziness, headache, dry mouth.

Miscellaneous

Impotence, sialadenitis.

Thiazides alone have been shown to cause the following additional adverse reactions:

Central Nervous System

Paresthesias, vertigo.

Ophthalmic

Xanthopsia, transient blurred vision.

Respiratory

Allergic pneumonitis, pulmonary edema, respiratory distress.

Other

Necrotizing vasculitis, exacerbation of lupus.

Hematologic

Aplastic anemia, agranulocytosis, hemolytic anemia.

Neonate and Infancy

Thrombocytopenia and pancreatitis – rarely, in newborns whose mothers have received thiazides during pregnancy.

Skin

Erythema multiforme, including Stevens-Johnson syndrome; exfoliative dermatitis, including toxic epidermal necrolysis.

Postmarketing Experience

Non-Melanoma Skin Cancer

Hydrochlorothiazide is associated with an increased risk of non-melanoma skin cancer. In a study conducted in the Sentinel System, increased risk was predominantly for squamous cell carcinoma (SCC) and in white patients taking large cumulative doses. The increased risk for SCC in the overall population was approximately 1 additional case per 16,000 patients per year, and for white patients taking a cumulative dose of ≥50,000 mg the risk increase was approximately 1 additional SCC case for every 6,700 patients per year.

To report SUSPECTED ADVERSE REACTIONS, contact Sandoz Inc. at 1-800-525-8747 or FDA at 1-800-FDA-1088 or www.fda.gov/medwatch.

DOSAGE AND ADMINISTRATION

The usual dose of triamterene and hydrochlorothiazide capsules is one or two capsules given once daily, with appropriate monitoring of serum potassium and of the clinical effect (see WARNINGS, Hyperkalemia).

OVERDOSAGE

Electrolyte imbalance is the major concern (see WARNINGS). Symptoms reported include: polyuria, nausea, vomiting, weakness, lassitude, fever, flushed face, and hyperactive deep tendon reflexes. If hypotension occurs, it may be treated with pressor agents such as levarterenol to maintain blood pressure. Carefully evaluate the electrolyte pattern and fluid balance. Induce immediate evacuation of the stomach through emesis or gastric lavage. There is no specific antidote.

Reversible acute renal failure following ingestion of 50 tablets of a product containing a combination of 50 mg triamterene and 25 mg hydrochlorothiazide has been reported.

Although triamterene is largely protein-bound (approximately 67%), there may be some benefit to dialysis in cases of overdosage.

HOW SUPPLIED

Capsules containing 37.5 mg triamterene, USP and 25 mg hydrochlorothiazide, USP are available for oral administration as white capsules with single black ink bands imprinted GG 606 in black ink and supplied as:

NDC 51655-722-52 bottles of 30

STORAGE AND HANDLING

Store at controlled room temperature 20°C to 25°C (68°F to 77°F) [see USP Controlled Room Temperature]. Protect from moisture. Protect from light.

Dispense in a tight, light-resistant container.

KEEP OUT OF REACH OF CHILDREN.

Manufactured by

Sandoz Private Ltd., India for

Sandoz Inc., Princeton, NJ 08540

Revised: 12/2025

Principal Display Panel

NDC: 51655-722-52